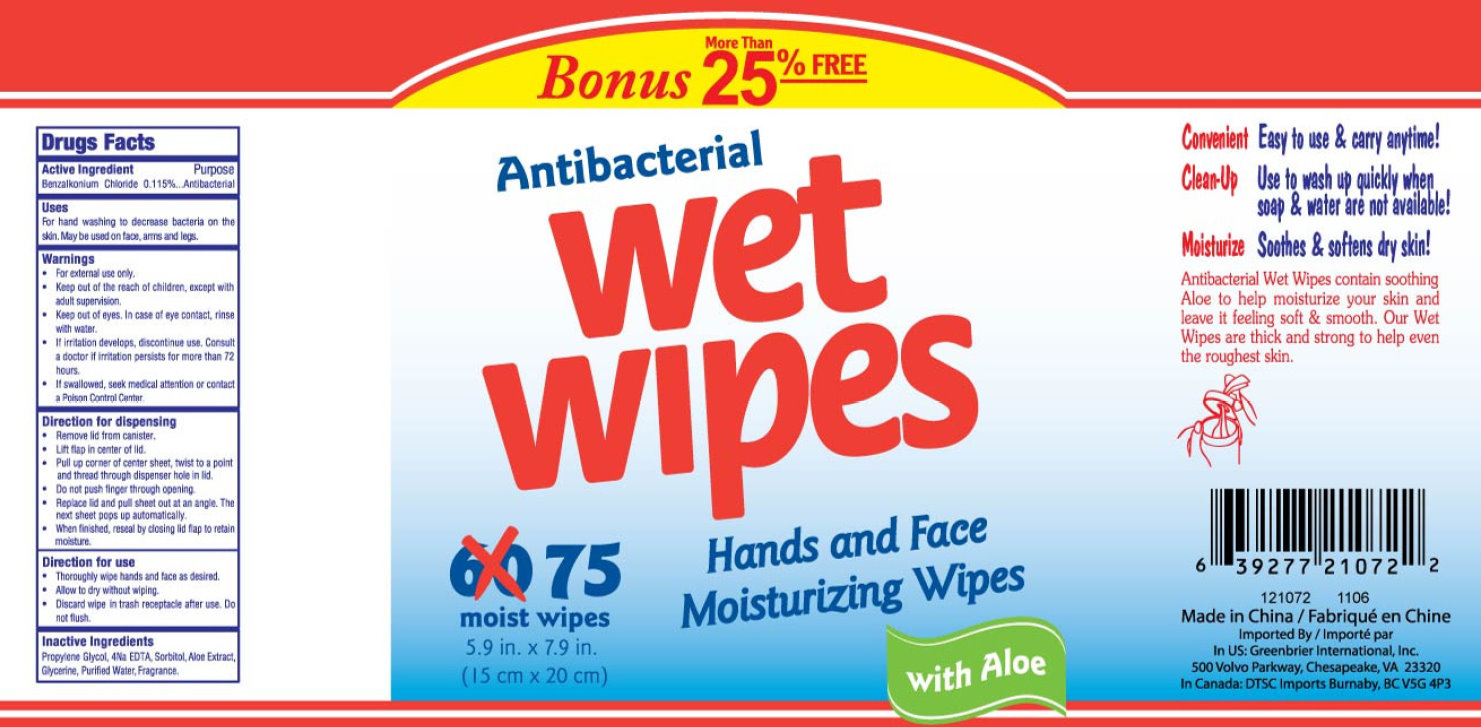 DRUG LABEL: Antibacterial Wet Wipes With Aloe
NDC: 33992-5000 | Form: LIQUID
Manufacturer: Greenbrier International, Inc.
Category: otc | Type: HUMAN OTC DRUG LABEL
Date: 20110530

ACTIVE INGREDIENTS: BENZALKONIUM CHLORIDE 0.115 g/100 g
INACTIVE INGREDIENTS: PROPYLENE GLYCOL; EDETIC ACID; SORBITOL; ALOE; WATER; GLYCERIN

Antibacterial Wet Wipes Hands and Face Moisturizing Wipes with Aloe

Active Ingredient

Benzalkonium chloride 0.115%

Purpose: Antibacterial

Uses

For hand washing to decrease bacteria on the skin. May be used on face, arms and legs.

Warnings

- For external use only.
- Keep out of eyes. In case of eye contact, rinse with water.
- If irritation develops, discontinue use. Consult a doctor if irritation persists more than 72 hours
- If swallowed, seek medical attention or contact a Poison Control Center.

KEEP OUT OF REACH OF CHILDREN

Keep out of the reach of children, except with adult supervision.

DOSAGE AND ADMINISTRATION

Direction for dispensing:

- Remove lid from canister.
- Lift flap in center of lid.
- Pull up corner of center sheet, twist to a point and thread through dispenser hole in lid.
- Do not push finger through opening.
- Replace lid and pull sheet out at an angle. The next sheet pops up automatically.
- When finished, reseal by closing lid flap to retain moisture.

Direction for use:

- Thoroughly wipe hands and face as desired.
- Allow to dry without wiping.
- Discard wipe in trash receptacle after use. Do not flush.

Inactive Ingredients

Propylene glycol, 4Na EDTA, Sorbitol, Aloe Extract, Glycerine, Purified Water, Fragrance.

PACKAGE LABEL

Convenient Easy to use and carry anytime!

Clean-Up Use to wash up quickly when soap and water are not available!

Moisturize Soothes and softens dry skin.

Antibacterial Wet Wipes contain soothing Aloe to help moisturize your skin and leave it feeling soft and smooth. Our Wet Wipes are thick and strong to help even the roughest skin.

Made in China

Imported by:

Greenbrier International, Inc.

500 Volvo Parkway

Chesapeake, VA 23320

In Canada: DTSC Imports Burnaby BC V5G 4P3

Bonus More Than 25% Free

Antibacterial Wet Wipes

75 moist wipes

5.9 in. x 7.9 in.

(15 cm x 20 cm)

Hands and Face Moisturizing Wipes

with Aloe